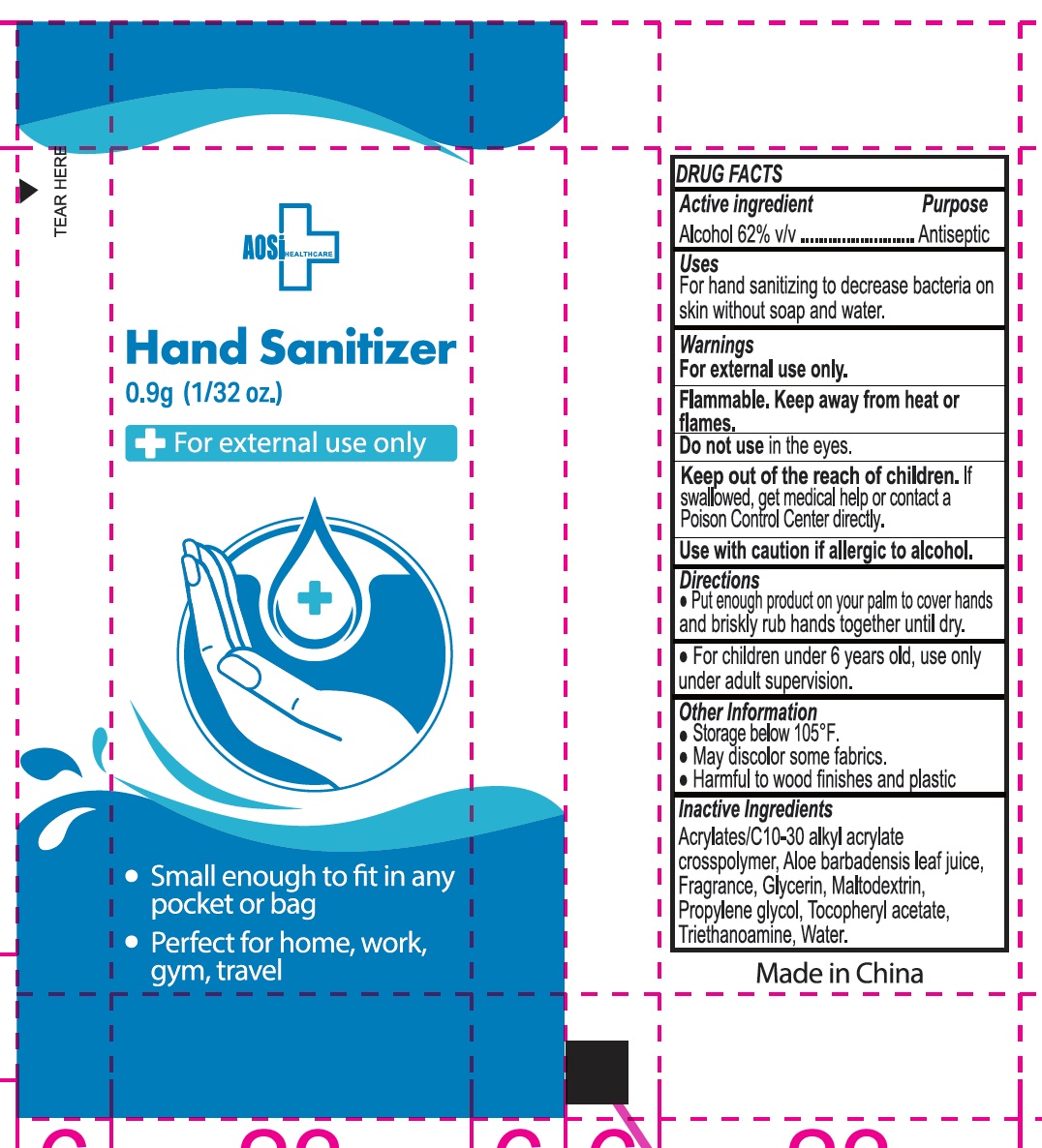 DRUG LABEL: AOSI HEALTHCARE HAND SANITIZER
NDC: 43473-056 | Form: GEL
Manufacturer: Nantong Health & Beyond Hygienic Products Inc.
Category: otc | Type: HUMAN OTC DRUG LABEL
Date: 20240925

ACTIVE INGREDIENTS: ALCOHOL 62 mL/100 mL
INACTIVE INGREDIENTS: WATER; GLYCERIN; PROPYLENE GLYCOL; ACRYLATES/C10-30 ALKYL ACRYLATE CROSSPOLYMER (60000 MPA.S); .ALPHA.-TOCOPHEROL ACETATE, D-; MALTODEXTRIN; ALOE VERA LEAF; TRICLOSAN

43473-056 AOSI Healthcare Hand Sanitizer

Active ingredient

Alcohol, 62% v/v

Purpose Antiseptic

Uses

- For hand sanitizing to decrease bacteria on the skin without soap and water

Warnings

For external use only.

Flammable, keep away from heat or flames

Do not use in the eyes

Use with caution if allergic to alcohol

Keep out of reach of children. If swallowed, get medical help or contact a Poison Control Center directly.

Directions:
• Put enough product on your palm to cover hands and briskly rub hands together until dry.
• For children under 6 years old, use only under adult supervision.

Other information

- Storage below 105°F.
- May discolor some fabrics.
- Harmful to wood finishes and plastic

Inactive ingredients

Acrylates/C10-30 alkyl acrylate crosspolymer, Aloe barbadensis leaf juice, Fragrance, Glycerin, Maltodextrin, Propylene glycol, Tocopheryl acetate,
Triethanoamine, Water